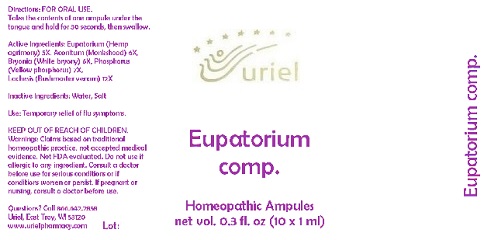 DRUG LABEL: Eupatorium comp.
NDC: 48951-4049 | Form: LIQUID
Manufacturer: Uriel Pharmacy Inc.
Category: homeopathic | Type: HUMAN OTC DRUG LABEL
Date: 20180517

ACTIVE INGREDIENTS: EUPATORIUM PERFOLIATUM FLOWERING TOP 5 [hp_X]/1 mL; ACONITUM NAPELLUS 6 [hp_X]/1 mL; BRYONIA ALBA ROOT 6 [hp_X]/1 mL; PHOSPHORUS 7 [hp_X]/1 mL; LACHESIS MUTA VENOM 12 [hp_X]/1 mL
INACTIVE INGREDIENTS: WATER; SODIUM CHLORIDE

Eupatorium comp.

INDICATIONS AND USAGE

Directions: FOR ORAL USE.

DOSAGE AND ADMINISTRATION

Take the contents of one ampule under the tongue and hold for 30 seconds, then swallow.

ACTIVE INGREDIENT

Active Ingredients: Eupatorium (Hemp agrimony) 5X, Aconitum (Monkshood) 6X, Bryonia (White bryony) 6X, Phosphorus (Yellow phosphorus) 7X,
Lachesis (Bushmaster venom) 12X

Inactive Ingredients: Water, Salt

PURPOSE

Use: Temporary relief of flu symptoms.

KEEP OUT OF REACH OF CHILDREN.

WARNINGS

Warnings: Claims based on traditional homeopathic practice, not accepted medical evidence. Not FDA evaluated. Do not use if allergic to any ingredient. Consult a doctor before use for serious conditions or if conditions worsen or persist. If pregnant or nursing, consult a doctor before use.

QUESTIONS

Questions? Call 866.642.2858 Uriel, East Troy, WI 53120 www.urielpharmacy.com